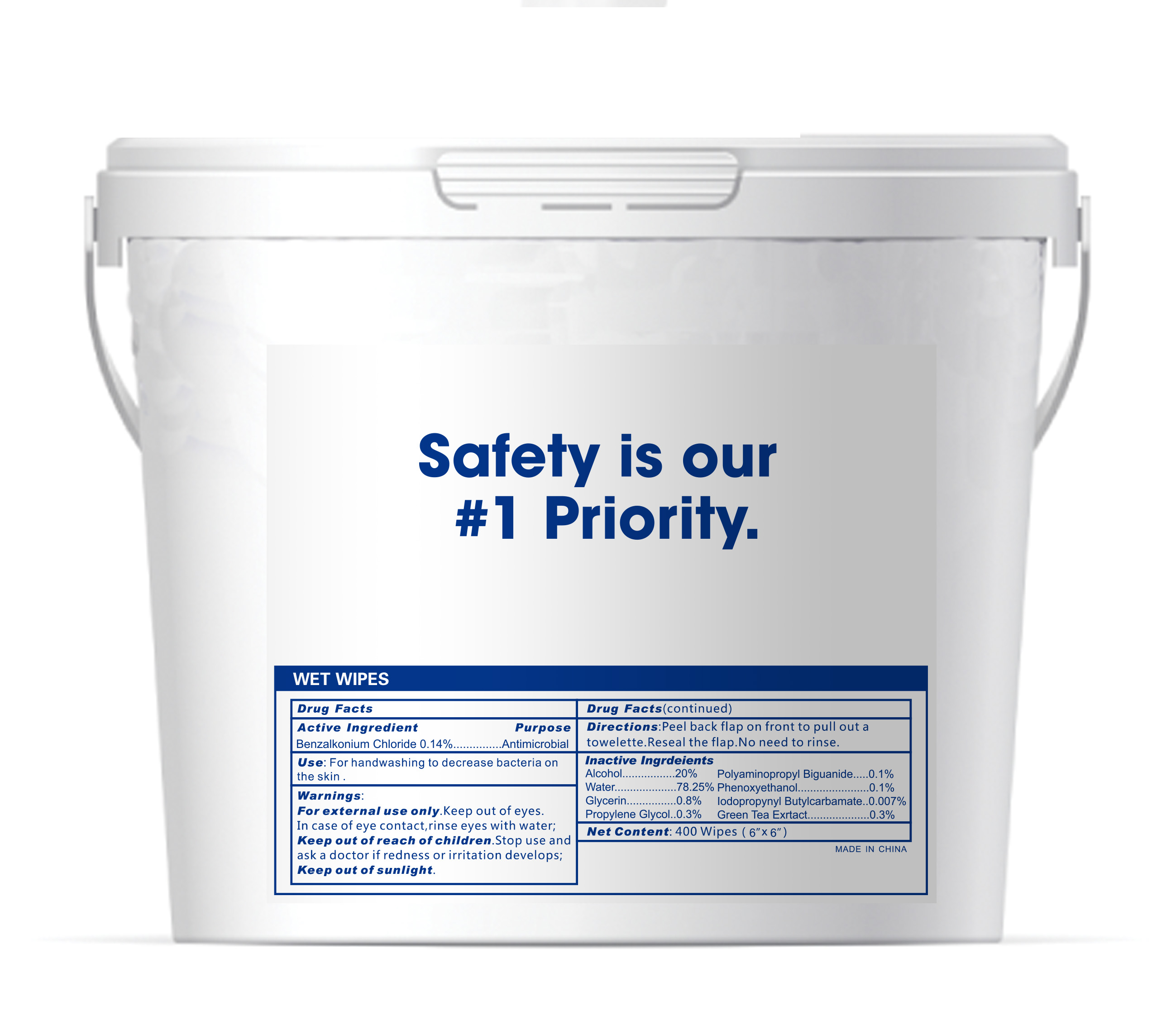 DRUG LABEL: Wet Wipes
NDC: 76635-007 | Form: CLOTH
Manufacturer: Hangzhou Glamcos Biotech CO.,LTD
Category: otc | Type: HUMAN OTC DRUG LABEL
Date: 20231123

ACTIVE INGREDIENTS: BENZALKONIUM CHLORIDE 0.14 g/100 g
INACTIVE INGREDIENTS: GREEN TEA LEAF; GLYCERIN; ALCOHOL; POLYAMINOPROPYL BIGUANIDE; PHENOXYETHANOL; PROPYLENE GLYCOL; WATER; IODOPROPYNYL BUTYLCARBAMATE

Active Ingredient(s)

Benzalkonium Chloride 0.14%

Purpose

Antimicrobial

Use

For handwashing to decrease bacteria on the skin.

Warnings

For external use only. Keep out of eyes.
In case of eye contact, rinse eyes with water.
Stop use and ask a doctor if redness or irritation develops.

Keep out of sunlight.

Keep out of reach of children.

Directions

Peel back flap on front to pull out a towelette. Reseal the flap. No need ro rinse.

Inactive ingredients

Alcohol………………….20% Polyaminopropyl Biguanide………………0.1%
Water…………………78.25% Phenoxyethanol…………………………...0.1%
Glycerin…………….. 0.8% Iodopropynyl Butylcarbamate……………0.007%
Propylene Glycol…….0.3% Green Tea Extract…………………………0.3%.